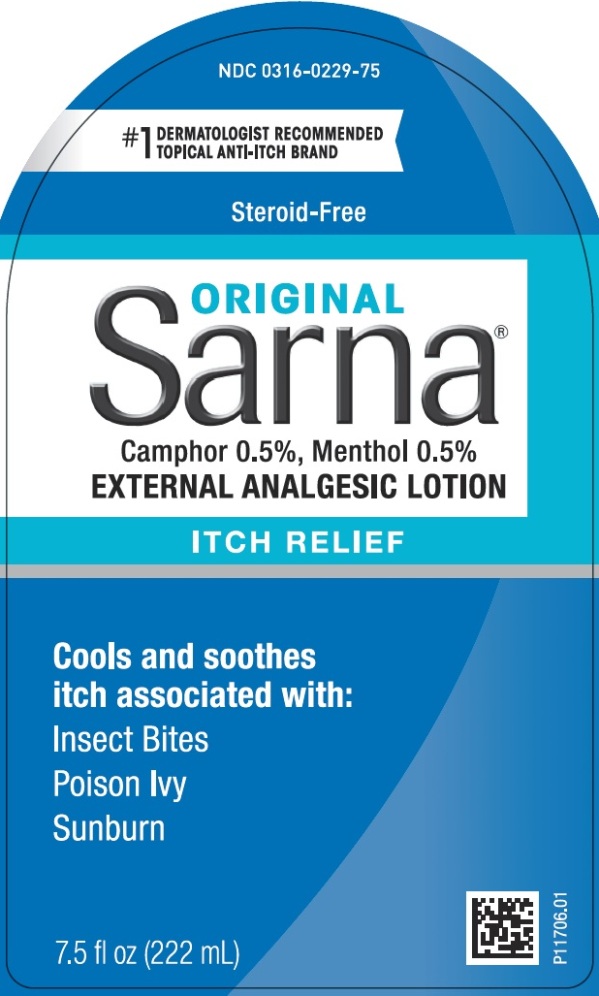 DRUG LABEL: Sarna
NDC: 0316-0229 | Form: LOTION
Manufacturer: Crown Laboratories
Category: otc | Type: HUMAN OTC DRUG LABEL
Date: 20240927

ACTIVE INGREDIENTS: CAMPHOR (SYNTHETIC) 5 mg/1 mL; MENTHOL, UNSPECIFIED FORM 5 mg/1 mL
INACTIVE INGREDIENTS: CARBOMER HOMOPOLYMER TYPE C (ALLYL PENTAERYTHRITOL CROSSLINKED); CETYL ALCOHOL; DMDM HYDANTOIN; GLYCERYL MONOSTEARATE; ISOPROPYL MYRISTATE; PETROLATUM; WATER; SODIUM HYDROXIDE; STEARIC ACID; POLYOXYL 8 STEARATE; POLYOXYL 100 STEARATE

Sarna Original

Active ingredients

Camphor 0.5%

Menthol 0.5%

Purpose

External analgesic

Uses

- for the temporary relief of pain and itching associated with minor burns, sunburn, minor cuts, scrapes, insect bites, minor skin irritations and rashes due to poison ivy, poison oak, or poison sumac

Warnings

For external use only

When using this product

- avoid contact with the eyes

Stop use and ask a doctor if

- condition worsens
- symptoms persist for more than 7 days or clear up and occur again within a few days.

If pregnant or breast-feeding,

ask a health care professional before use.

Keep out of reach of children.

If swallowed, get medical help or contact a Poison Control Center right away.

Directions

- to open, hold cap tightly and turn pump counter-clockwise

Adults and children 2 years of age and older:

- apply to affected area not more than 3 to 4 times daily

Children under 2 years of age:

- consult a doctor

Other information

- Store at 20o - 25oC (68o - 77oF) [see USP Controlled Room Temperature].

Inactive ingredients

carbomer homopolymer type C, cetyl alcohol, DMDM hydantoin, fragrance, glyceryl monostearate, isopropyl myristate, petrolatum, PEG-8 stearate, PEG-100 stearate, purified water, sodium hydroxide, stearic acid

Questions or comments?

Call 1-833-279-6522

RECENT MAJOR CHANGES

Formatted Uses section

Foramtted Directions section

Principal Display Panel

NDC 0316-0229-75

#1 DERMATOLOGIST RECOMMENDED TOPICAL ANTI-ITCH BRAND

Steroid-Free

Sarna ORIGINAL

Camphor 0.5%, Menthol 0.5%

EXTERNAL ANALGESIC LOTION

ITCH RELIEF

Cools and soothes itch associated with:

Insect Bites

Poison Ivy

Sunburn

Net wt. 7.5 fl oz (222 mL)

P11706.01

Sarna is registered trademark of Crown Laboratories, Inc.

Distributed by: Crown Laboratories, Inc., Johnson City, TN 37604

©2019 Crown Laboratories, Inc.